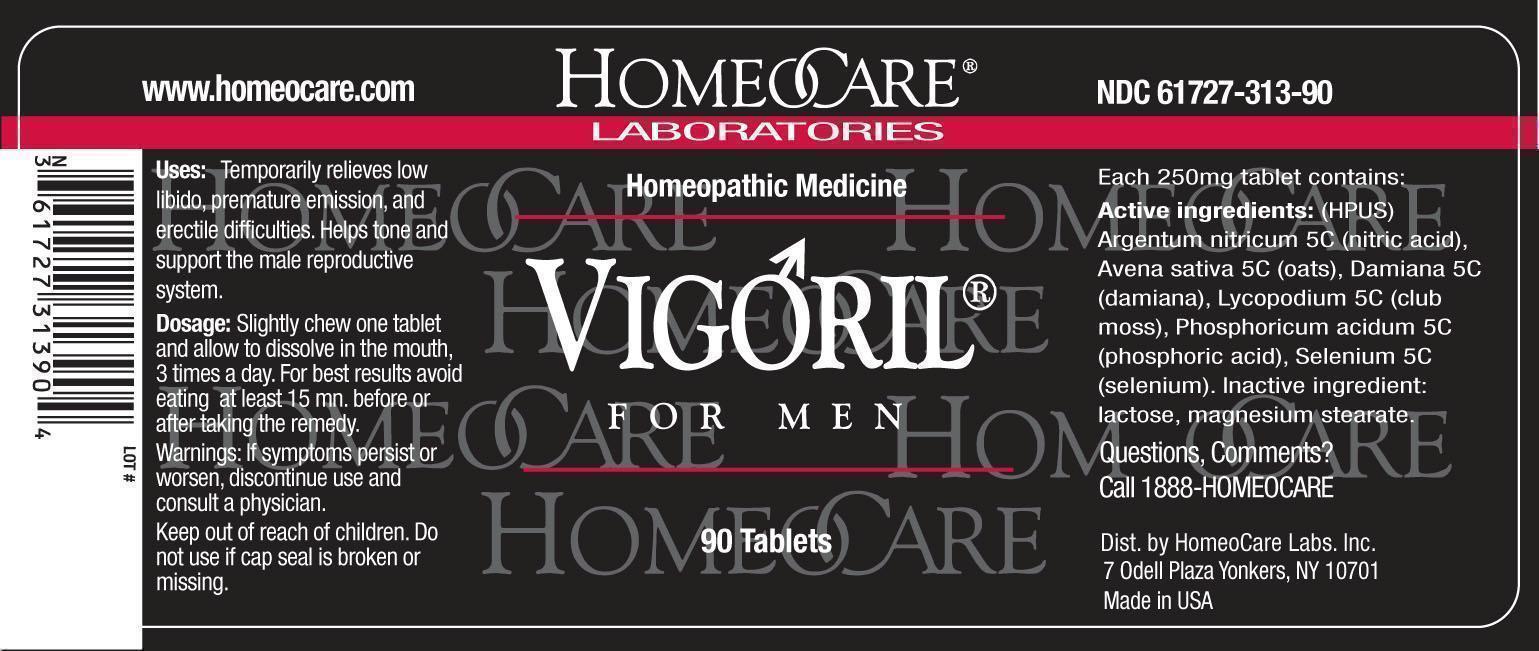 DRUG LABEL: Vigoril for Men
NDC: 61727-313 | Form: TABLET
Manufacturer: HomeoCare Laboratories, Inc.
Category: homeopathic | Type: HUMAN OTC DRUG LABEL
Date: 20181226

ACTIVE INGREDIENTS: SILVER NITRATE 5 [hp_C]/1 1; AVENA SATIVA FLOWERING TOP 5 [hp_C]/1 1; LYCOPODIUM CLAVATUM SPORE 5 [hp_C]/1 1; PHOSPHORIC ACID 5 [hp_C]/1 1; SELENIUM 5 [hp_C]/1 1; TURNERA DIFFUSA LEAFY TWIG 5 [hp_C]/1 1
INACTIVE INGREDIENTS: MAGNESIUM STEARATE; LACTOSE, UNSPECIFIED FORM

Vigoril for Men

Inactive ingredient:

Lactose, Magnesium Stearate

Active ingredients: (HPUS)

Argentum nitricum 5C (nitric acid), Avena sativa 5C (oats), Damiana 5C (damiana), Lycopodium 5C (club moss), Phosphoricum acidum 5C (phosphoric acid), Selenium 5C (selenium).

Uses:

Temporarily relieves low libido, premature emission, and erectile difficulties. Helps tone and support the male reproductive system.

Dosage:

Slightly chew one tablet and allow to dissolve in the mouth, 3 times a day. For best results avoid eating at least 15 min. before or after taking the remedy.

Warnings:

If symptoms persist or worsen, discontinue use and consult a physician.

Keep out of reach of children. Do not use if cap seal is broken or missing.

Warnings:

Keep out of reach of children.

Questions, Comments?

Call 1888-HOMEOCARE

Dist. by HomeoCare Labs, Inc.

7 Odell Plaza Yonkers, NY 10701

Made in USA

Uses: Dosage:

Temporarily relieves low libido, premature emission, and erectile difficulties. Helps tone and support the male reproductive system.

Slightly chew one tablet and allow to dissolve in the mouth, 3 times a day. For best results avoid eating at least 15 mn. before or after taking the remedy.